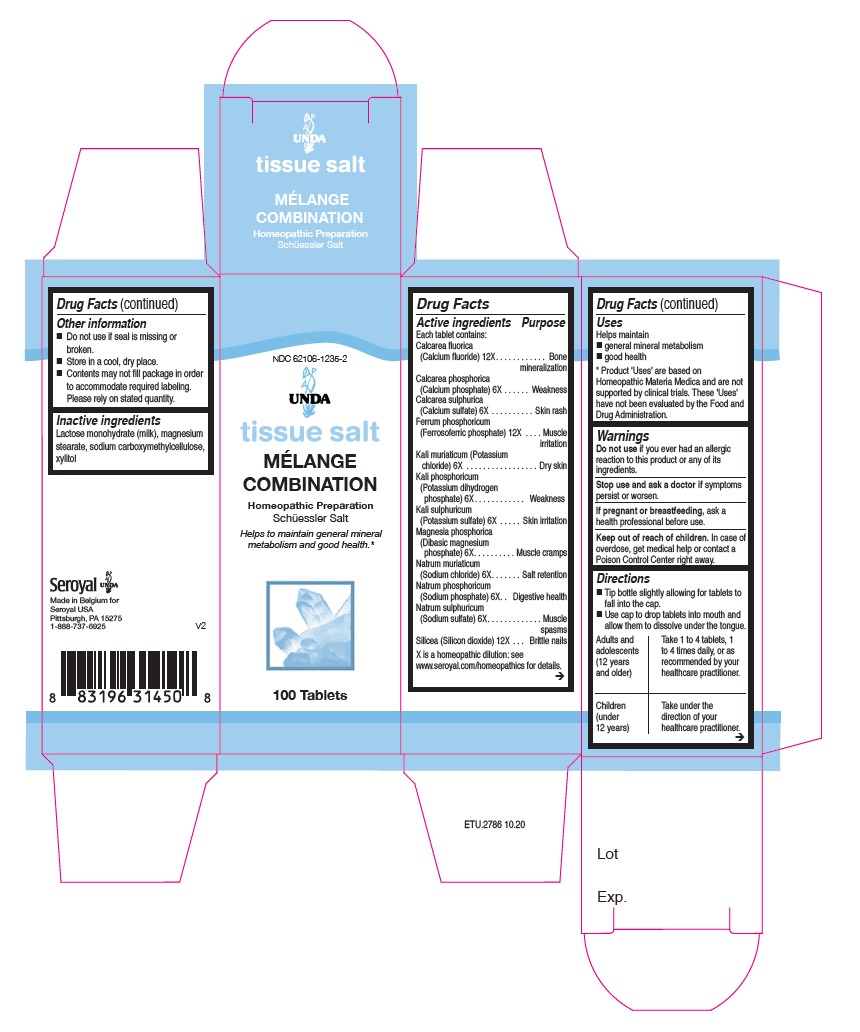 DRUG LABEL: Melange combination
NDC: 62106-1235 | Form: TABLET
Manufacturer: Seroyal USA
Category: homeopathic | Type: HUMAN OTC DRUG LABEL
Date: 20210714

ACTIVE INGREDIENTS: CALCIUM PHOSPHATE, DIBASIC, ANHYDROUS 6 [hp_X]/1 1; POTASSIUM CHLORIDE 6 [hp_X]/1 1; POTASSIUM PHOSPHATE, DIBASIC 6 [hp_X]/1 1; CALCIUM SULFATE ANHYDROUS 6 [hp_X]/1 1; SODIUM PHOSPHATE, DIBASIC, HEPTAHYDRATE 6 [hp_X]/1 1; SILICON DIOXIDE 12 [hp_X]/1 1; POTASSIUM SULFATE 6 [hp_X]/1 1; MAGNESIUM PHOSPHATE, DIBASIC TRIHYDRATE 6 [hp_X]/1 1; SODIUM CHLORIDE 6 [hp_X]/1 1; SODIUM SULFATE 6 [hp_X]/1 1; CALCIUM FLUORIDE 12 [hp_X]/1 1; FERROSOFERRIC PHOSPHATE 12 [hp_X]/1 1
INACTIVE INGREDIENTS: LACTOSE MONOHYDRATE; XYLITOL; CROSCARMELLOSE SODIUM; MAGNESIUM STEARATE

Melange Tissue Salt

Active Ingredients

Each Tablet Contains:

Calcarea fluorica (Calcium fluoride) 12X
Calcarea phosphorica (Calcium phosphate) 6X
Calcarea sulphurica (Calcium sulfate) 6X
Ferrum phosphoricum (Ferrosoferric phosphate) 12X
Kali muriaticum (Potassium chloride) 6X
Kali phosphoricum (Dibasic potassium phosphate) 6X
Kali sulphuricum (Potassium sulfate) 6X
Magnesia phosphorica (Dibasic magnesium phosphate) 6X
Natrum muriaticum (Sodium chloride) 6X
Natrum phosphoricum (Sodium phosphate) 6X
Natrum sulphuricum (Sodium sulfate) 6X
Silicea (Silicon dioxide) 12X

Uses
Helps to maintain general mineral metabolism and good health.

Warnings
Do not use if you ever had an allergic reaction to this product or any of its ingredients.
Stop use and ask a doctor if symptoms persist or worsen.
If pregnant or breastfeeding, ask a health professional before use.
Keep out of reach of children.

In case of overdose, get medical help or contact a Poison Control Center right away.

Keep out of reach of children.

OVERDOSAGE

In case of overdose, get medical help or contact
a Poison Control Center right away.

Stop use and ask a doctor if symptoms persist or worsen.

Inactive ingredients
Lactose monohydrate (milk), magnesium
stearate, sodium carboxymethylcellulose,
xylitol

Directions
Tip bottle slightly allowing for tablets to fall into the cap.
Use cap to drop tablets into mouth and allow them to dissolve under the tongue.
Adults and adolescents (12 years and older): Take 1 to 4 tablets, one to four times daily or as recommended by your healthcare practitioner.

Children (under 12 years): Take under the direction of your healthcare practitioner.

Uses
Helps to maintain general mineral metabolism and good health.

Directions

Tip bottle slightly allowing for tablets to fall into the cap.
Use cap to drop tablets into mouth and allow them to dissolve under the tongue.
Adults and adolescents (12 years and older): Take 1 to 4 tablets, one to four times daily, or as recommended
by your healthcare practitioner.

Children (under 12 years): Take under the direction of your healthcare practitioner.

Other information
Do not use if seal is missing or broken.
Store in a cool, dry place

Contents may not fill package in order
to accommodate required labeling.
Please rely on stated quantity.

PACKAGE LABEL

NDC 62106-1235-2

UNDA

tissue salt

MÉLANGE COMBINATION

Homeopathic Preparation
Schüessler Salt
Helps to maintain general mineral metabolism and good health.

100 Tablets